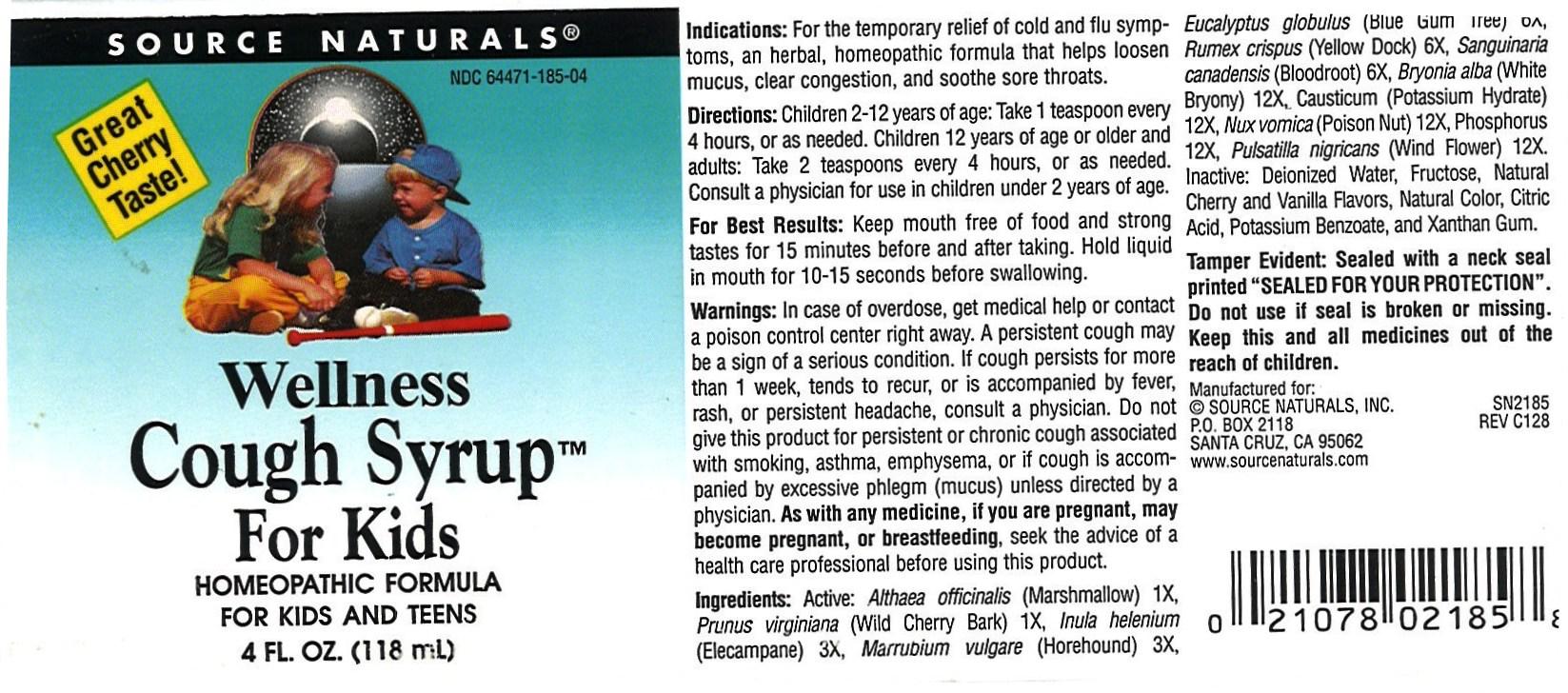 DRUG LABEL: Wellness with Cherry Flavor
NDC: 64471-185 | Form: SYRUP
Manufacturer: Source Naturals
Category: homeopathic | Type: HUMAN OTC DRUG LABEL
Date: 20131016

ACTIVE INGREDIENTS: ALTHAEA OFFICINALIS ROOT 1 [hp_X]/118 mL; PRUNUS VIRGINIANA BARK 1 [hp_X]/118 mL; INULA HELENIUM ROOT 3 [hp_X]/118 mL; MARRUBIUM VULGARE 3 [hp_X]/118 mL; EUCALYPTUS GLOBULUS LEAF 6 [hp_X]/118 mL; RUMEX CRISPUS ROOT 6 [hp_X]/118 mL; SANGUINARIA CANADENSIS ROOT 6 [hp_X]/118 mL; BRYONIA ALBA WHOLE 12 [hp_X]/118 mL; CAUSTICUM 12 [hp_X]/118 mL; STRYCHNOS NUX-VOMICA SEED 12 [hp_X]/118 mL; PHOSPHORUS 12 [hp_X]/118 mL; Anemone nemorosa 12 [hp_X]/118 mL
INACTIVE INGREDIENTS: WATER ; FRUCTOSE; CHERRY JUICE; VANILLA; NATURAL RED 26; CITRIC ACID MONOHYDRATE; POTASSIUM BENZOATE; XANTHAN GUM

Wellness Cough Syrup

Active Ingredients:

- Althaea officinalis 1x
- Prunus virginiana 1x
- Inula helenium 3x
- Marrubium vulgare 3x
- Eucalyptus globulus 6x
- Rumex crispus 6x
- Sanguinaria canadensis 6x
- Bryonia alba 12x
- Causticum 12x
- Nux vomica 12x
- Phosphorus 12x
- Pulsatilla nigricans 12x

PURPOSE

- Homeopathic cough syrup for kids and teens

- Keep out of reach of children

INDICATIONS AND USAGE

- For the temporary relief of coughs and congestion due to cold and flu.
- Helps loosen mucus (expectorant) and clear bronchial congestion.
- Soothes sore throat.

- For best Results:

-
  - Keep mouth free of food and strong tastes for 15 minutes before and after taking.
-
  - Hold liquid in mouth for 10-15 seconds before swallowing.

WARNINGS

- In case of overdose get medical help or contact poison control center right away
- A persistent cough may be a sign of a serious condition
- If cough persists for more than 1 week, tends to recur, or is accompanied by fever, rash, or persistent headache, consult a physician
- Do not give this product for persistent or chronic cough associate with smoking, asthma, emphysema, or if cough is accompanied by excessive phlegm (mucus) unless directed by a physician
- As with any medicine, if you are pregnant, may become pregnant, or breasfeeding, seek the advice of a health care professional before using this product

DOSAGE AND ADMINISTRATION

- Adults and children 12 years of age and older:
-
  - Take 2 teaspoons every 4 hours
  - Or as needed

- Children 2 - 12 years of age:
-
  - Take 1 teaspoon every 4 hours
  - Or as needed

- Children under 2: Consult a physician for use

Inactive Ingredients:

- Deionized water
- Fructose
- Natural Cherry flavor
- Vanilla flavor
- Natural color
- Citric acid
- Potassium Benzoate
- Xanthan gum

PACKAGE LABEL

- bottle image jpeg
- bottlelabel/.jpg